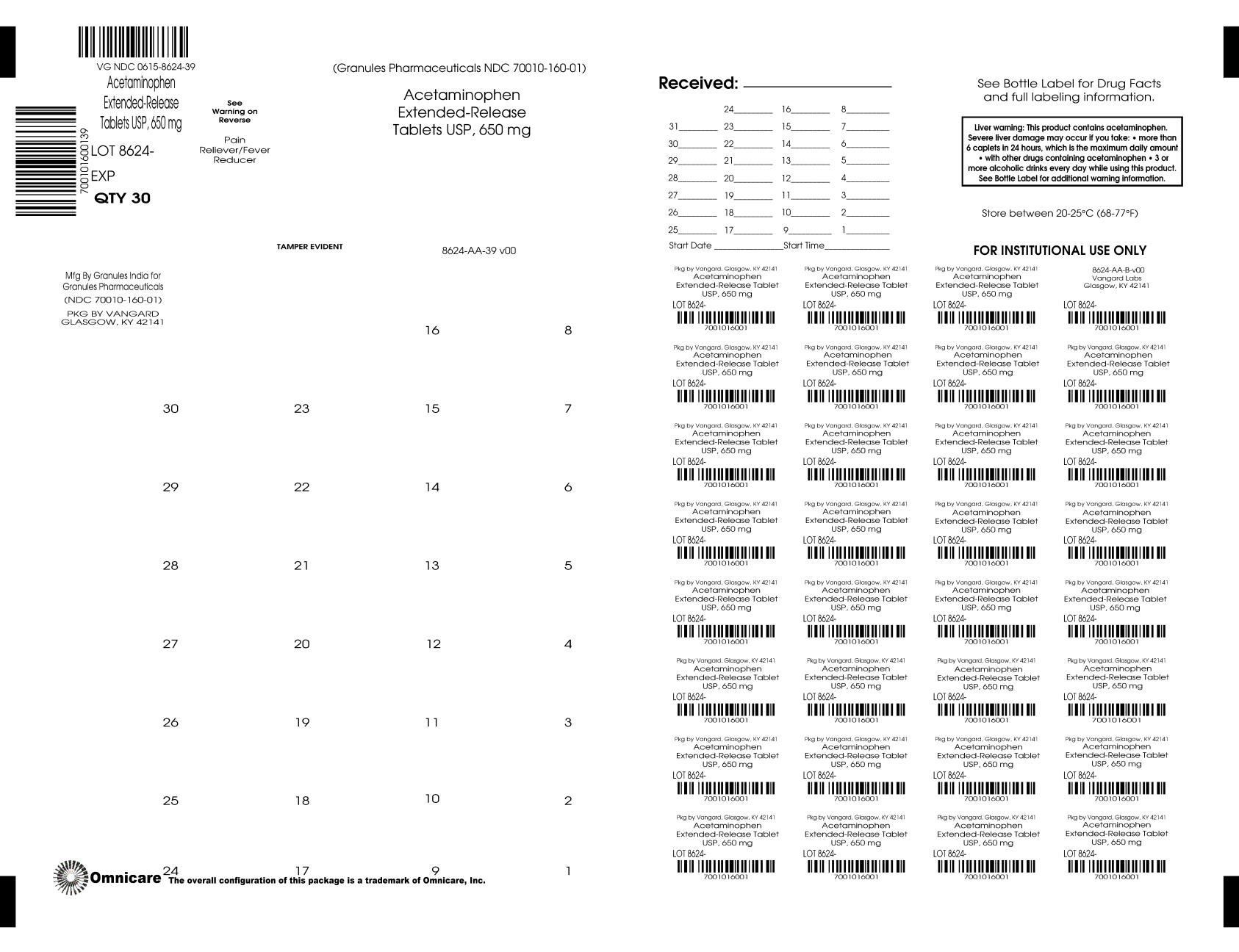 DRUG LABEL: ACETAMINOPHEN
NDC: 0615-8624 | Form: TABLET, EXTENDED RELEASE
Manufacturer: NCS HealthCare of KY, LLC dba Vangard Labs
Category: otc | Type: HUMAN OTC DRUG LABEL
Date: 20260226

ACTIVE INGREDIENTS: ACETAMINOPHEN 650 mg/1 1
INACTIVE INGREDIENTS: HYPROMELLOSE 2910 (6 MPA.S); MAGNESIUM STEARATE; POVIDONE K30; STARCH, CORN; STEARIC ACID; SODIUM STARCH GLYCOLATE TYPE A CORN; HYDROXYETHYL CELLULOSE (140 CPS AT 5%); MICROCRYSTALLINE CELLULOSE; POLYETHYLENE GLYCOL 400

Acetaminophen Extended Release Tablets 650 mg

ACTIVE INGREDIENT (IN EACH CAPLET)

Acetaminophen USP, 650 mg

PURPOSE

Pain reliever/fever reducer

USES

• temporarily relieves minor aches and pains due to:
• minor pain of arthritis
• muscular aches
• backache
• premenstrual and menstrual cramps
• the common cold
• headache
• toothache
• temporarily reduces fever

WARNINGS

Liver warning: This product contains acetaminophen. Severe Liver damage may occur if you take
• more than 6 caplets in 24 hours, which is the maximum daily amount
• with other drugs containing acetaminophen
• 3 or more alcoholic drinks everyday while using this product

Allergy alert: acetaminophen may cause severe skin reactions
Symptoms may include:
• skin reddening
• blisters
• rash
If a skin reaction occurs, stop use and seek medical help right away

Do not use

• with any other drugs containing acetaminophen (prescription or nonprescription). If you are not sure whether a drug contains acetaminophen, ask a doctor or pharmacist.
• if you are allergic to acetaminophen or any of the inactive ingredients in this product.

Ask a doctor before use if you have

liver disease.

Ask a doctor or pharmacist before use if you are

taking the blood thinning drug warfarin.

Stop use and ask doctor if

• pain gets worse or lasts more than 10 days
• fever gets worse or lasts more than 3 days
• new symptoms occur
• redness or swelling is present
These could be signs of a serious condition.

If pregnant or breast-feeding

ask a health professional before use.

Keep out of reach of children

Overdose warning: In case of overdose, get medical help or contact a poison control center right away.(1-800 222-1222). Quick medical attention is critical for adults as well as for children even if you do not notice any signs or symptoms

DIRECTIONS

• do not take more than directed (see overdose warning)

adults | • take 2 caplets every 8 hours with water • swallow whole; do not crush, chew, split or dissolve • do not take more than 6 caplets in 24 hours • do not use for more than 10 days unless directed by a doctor
under 18 years of age | • ask a doctor

OTHER INFORMATION

• store between 20-25°C (68-77°F)
• do not use if foil inner seal is broken or missing.

INACTIVE INGREDIENTS

hydroxyethyl cellulose, hypromellose, magnesium stearate, microcrystalline cellulose, polyethylene glycol, povidone, pregelatinized starch, sodium starch glycolate, stearic acid

QUESTIONS OR COMMENTS ?

Contact 1-877-770-3183 Mon-Fri 8:00 AM EST to 5:00 PM PST.